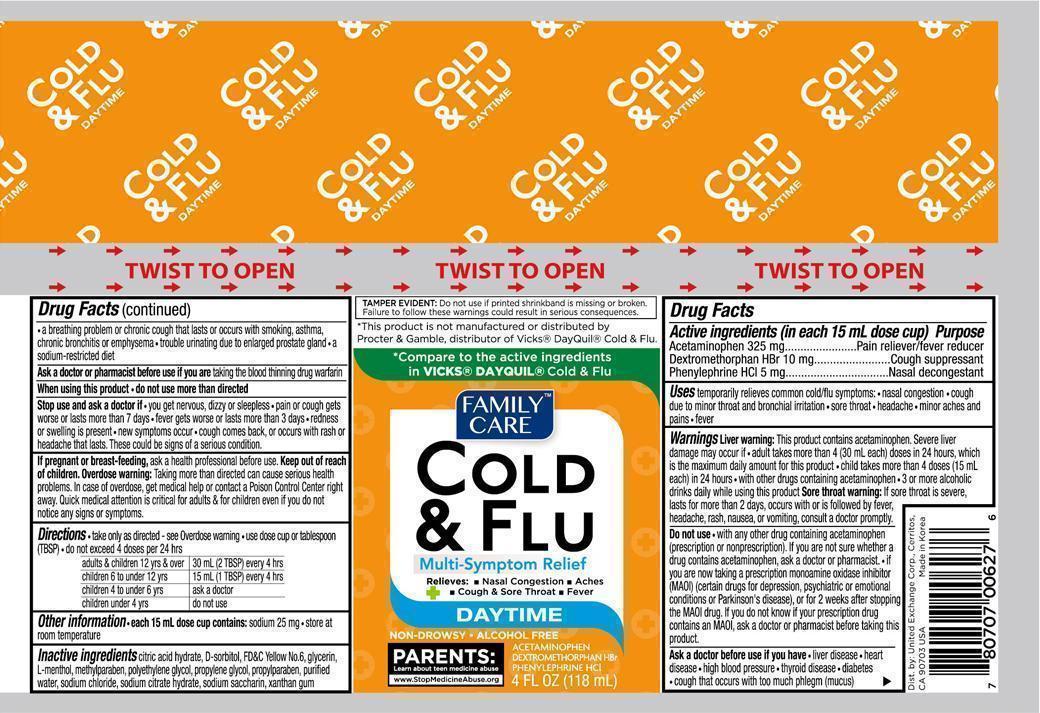 DRUG LABEL: Family Care Cold and Flu Multi Symptom
NDC: 65923-627 | Form: LIQUID
Manufacturer: United Exchange Corp.
Category: otc | Type: HUMAN OTC DRUG LABEL
Date: 20150723

ACTIVE INGREDIENTS: ACETAMINOPHEN 325 mg/15 mL; DEXTROMETHORPHAN HYDROBROMIDE 10 mg/15 mL; PHENYLEPHRINE HYDROCHLORIDE 5 mg/15 mL
INACTIVE INGREDIENTS: CITRIC ACID MONOHYDRATE; SORBITOL; FD&C YELLOW NO. 6; GLYCERIN; MENTHOL; METHYLPARABEN; POLYETHYLENE GLYCOLS; PROPYLENE GLYCOL; PROPYLPARABEN; WATER; SODIUM CHLORIDE; SODIUM CITRATE; SACCHARIN SODIUM; XANTHAN GUM

ACTIVE INGREDIENT

Active ingredients (in each 15 mL dose cup) Purpose

Acetaminophen 325 mg................................................Pain reliever/fever reducer

Dextromethorphan HBr 10 mg..................................................cough suppressant

Phenylephrine HCI 5 mg.........................................................Nasal decongestant

PURPOSE

Uses temporarily relieves common cold/flu symptoms:

- nasal congestion
- cough due to minor throat and bronchial irritation
- sore throat
- headache
- minor aches and pains
- fever

Warnings

Liver warning: This product contains acetaminophen. Sever liver damage may occur if

- adult takes more than 4 (30 mL each) doses in 24 hours, which is the maximum daily amount for this product
- child takes more than 4 doses (15 mL each) in 24 hours
- with other drugs containing acetaminophen
- 3 or more alcoholic drinks daily while using this product

Sore throat warning: if sore throat is sever, lasts more than 2 days, occurs with or is followed by fever, headache, rash, nausea, or vomiting, consult a doctor promptly.

Do not use

- with any other drug containing acetaminophen (prescription or nonprescription). If you are not sure whether a drug contains acetaminophen, ask a doctor or pharmacist.
- if you are now taking a prescription monoamine oxidase inhibitor (MAOI) (certain drugs for depression, psychiatric or emotional conditions or Parkinson's disease), or for 2 weeks after stopping the MAOI drug. If you do not know if your prescription drug contains an MAOI, ask a doctor or pharmacist before taking this product.

Ask a doctor before use if you have

- liver disease
- heart disease
- high blood pressure
- thyroid disease
- diabetes
- cough that occurs with too much phlegm (mucus)
- a breathing problem or chronic cough that lasts or occurs with smoking, asthma, chronic bronchitis or emphysema
- trouble urinating due to enlarged prostate gland
- a sodium-resitricted diet

Ask a doctor or pharmacist before use if you are taking the blood thinning drug warfarin

When using this product

- do not use more than directed

Stop use and ask a doctor if

- you get nervous, dizzy or sleepless
- pain or cough gets worse or lasts more than 7 days
- fever gets worse or lasts more than 3 days
- redness or swelling is present
- new symptoms occur
- cough comes back, or occurs with rash or headache that lasts. These could be signs of a serious condition.

PREGNANCY OR BREAST FEEDING

If pregnant or breast-feeding, ask a health professional before use.

Keep out of reach of children. Overdose warning: Taking more than directed can cause serious health problems. In case of overdose, get medical help or contact a Poison Control Center right away. Quick medical attention is critical for adults & for children even if you do not notice any signs or symptoms.

Directions

- take only as directed - see Overdose warning
- use dose cup or tablespoon (TBSP)
- do not exceed 4 doses per 24 hrs

adults & children 12 yrs over: 30 mL (2TBSP) every 4 hours

children 6 to under 12 yrs: 15 mL(1 TBSP) every 4 hours

children 4 to under 6 yrs: ask a doctor

children under 4 yrs: do not use

Other information

- each 15 mL dose cup contains: sodium 25 mg
- store at room temperature

Inactive ingredients

citric acid hydrate, D-sorbitol, FD&C Yellow No. 6, glycerin, L-menthol, methylparaben, polyethylene glycol, propylene glycol, propylparaben, purified water, sodium chloride, sodium citrate hydrate, sodium saccharin, xanthan gum

DOSAGE AND ADMINISTRATION

Distributed by:

United Exchange Corp.

17211 Valley View Ave.

Cerritos, CA 90703

Made in Korea